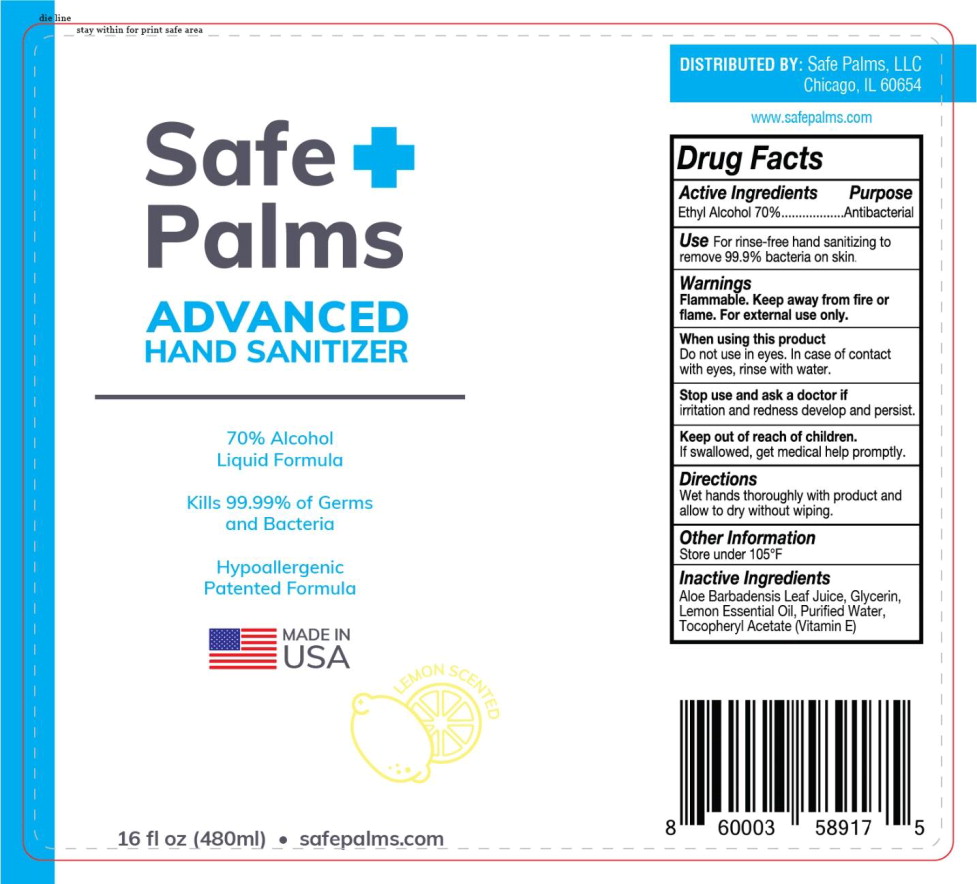 DRUG LABEL: Advanced Hand Sanitizer
NDC: 90117-101 | Form: LIQUID
Manufacturer: Safe Palms, LLC
Category: otc | Type: HUMAN OTC DRUG LABEL
Date: 20200825

ACTIVE INGREDIENTS: ALCOHOL 70 mL/100 mL
INACTIVE INGREDIENTS: ALOE VERA LEAF; GLYCERIN; WATER; .ALPHA.-TOCOPHEROL ACETATE; Lemon Oil

Drug Facts

Active Ingredients

Ethyl Alcohol 70%

Purpose

Antibacterial

Use

For rinse-free hand sanitizing to remove 99.9% bacteria on skin

Warnings

Flammable. Keep away from fire or flame. For external use only.

When using this product

Do not use in eyes. In case of contact with eyes, rinse with water.

Stop use and ask a doctor if irritation and redness develop and persist.

Keep out of reach of children.

If swallowed, get medical help promptly.

Directions

Wet hands thoroughly with product and allow to dry without wiping.

Other Information

Store under 105°F

Inactive Ingredients

Aloe Barbadensis Leaf Juice, Glycerin, Lemon Essential Oil, Purified Water, Tocopheryl Acetate (Vitamin E)

PACKAGE LABEL

Safe +
Palms

ADVANCED
HAND SANITIZER

70% Alcohol

Liquid Formula

Kills 99.99% of Germs
and Bacteria

Hypoallergenic
Patented Formula

MADE IN
USA

LEMON SCENTED

16 fl oz (480ml) • safepalms.com